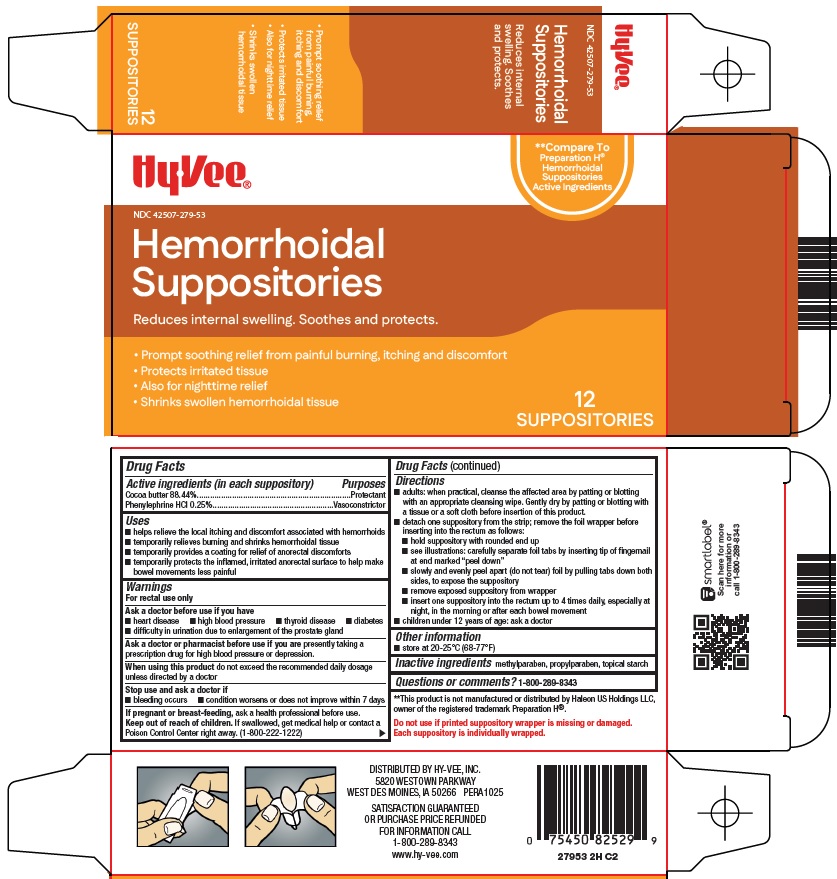 DRUG LABEL: hemorrhoidal
NDC: 42507-279 | Form: SUPPOSITORY
Manufacturer: HyVee Inc
Category: otc | Type: HUMAN OTC DRUG LABEL
Date: 20260121

ACTIVE INGREDIENTS: COCOA BUTTER 2211 mg/1 1; PHENYLEPHRINE HYDROCHLORIDE 6.5 mg/1 1
INACTIVE INGREDIENTS: METHYLPARABEN; PROPYLPARABEN; STARCH, CORN

Hy-Vee, Inc. Hemorrhoidal Suppositories Drug Facts

Active ingredients (in each suppository)

Cocoa butter 88.44%

Phenylephrine HCl 0.25%

Purposes

Protectant

Vasoconstrictor

Uses

- helps relieve the local itching and discomfort associated with hemorrhoids
- temporarily relieves burning and shrinks hemorrhoidal tissue
- temporarily provides a coating for relief of anorectal discomforts
- temporarily protects the inflamed, irritated anorectal surface to help make bowel movements less painful

Warnings

For rectal use only

Ask a doctor before use if you have

- heart disease
- high blood pressure
- thyroid disease
- diabetes
- difficulty in urination due to enlargement of the prostate gland

Ask a doctor or pharmacist before use if you are

presently taking a prescription drug for high blood pressure or depression.

When using this product

do not exceed the recommended daily dosage unless directed by a doctor

Stop use and ask a doctor if

- bleeding occurs
- condition worsens or does not improve within 7 days

If pregnant or breast feeding,

ask a health professional before use.

Keep out of reach of children.

If swallowed, get medical help or contact a Poison Control Center right away. (1-800-222-1222)

Directions

- adults: when practical, cleanse the affected area by patting or blotting with an appropriate cleansing wipe. Gently dry by patting or blotting with a tissue or a soft cloth before insertion of this product.
- detach one suppository from the strip; remove the foil wrapper before inserting into the rectum as follows:
- hold suppository with rounded end up
- see illustrations: carefully separate foil tabs by inserting tip of fingernail at end marked “peel down”
- slowly and evenly peel apart (do not tear) foil by pulling tabs down both sides, to expose the suppository
- remove exposed suppository from wrapper
- insert one suppository into the rectum up to 4 times daily, especially at night, in the morning or after each bowel movement
- children under 12 years of age: ask a doctor

Other information

- store at 20-25°C (68-77°F)

Inactive ingredients

methylparaben, propylparaben, topical starch

Questions or comments?

1-800-289-8343

Package/Label Principal Display Panel

Hy•Vee®

Compare to Preparation H® Hemorrhoidal Suppositories Active Ingredients

Hemorrhoidal Suppositories

Reduces internal swelling. Soothes and protects.

• Prompt soothing relief from painful burning, itching and discomfort

• Protects irritated tissue

• Also for nighttime relief

• Shrinks swollen hemorrhoidal tissue

12 SUPPOSITORIES